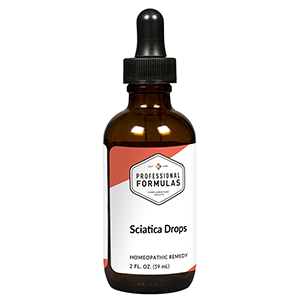 DRUG LABEL: Sciatica Drops
NDC: 63083-2059 | Form: LIQUID
Manufacturer: Professional Complementary Health Formulas
Category: homeopathic | Type: HUMAN OTC DRUG LABEL
Date: 20190815

ACTIVE INGREDIENTS: BERBERIS VULGARIS ROOT BARK 3 [hp_X]/59 mL; POTASSIUM IODIDE 3 [hp_X]/59 mL; RUTA GRAVEOLENS FLOWERING TOP 3 [hp_X]/59 mL; AMMONIUM CATION 4 [hp_X]/59 mL; ACONITUM NAPELLUS WHOLE 6 [hp_X]/59 mL; AMARYLLIS BELLADONNA WHOLE 6 [hp_X]/59 mL; BELLIS PERENNIS WHOLE 6 [hp_X]/59 mL; CITRULLUS COLOCYNTHIS FRUIT PULP 6 [hp_X]/59 mL; PSEUDOGNAPHALIUM OBTUSIFOLIUM WHOLE 6 [hp_X]/59 mL; STRYCHNOS NUX-VOMICA SEED 6 [hp_X]/59 mL; SPIGELIA ANTHELMIA WHOLE 6 [hp_X]/59 mL; ARSENIC TRIOXIDE 12 [hp_X]/59 mL; CAUSTICUM 12 [hp_X]/59 mL; HYPERICUM PERFORATUM WHOLE 30 [hp_X]/59 mL
INACTIVE INGREDIENTS: ALCOHOL; WATER

C59

ACTIVE INGREDIENTS

Berberis vulgaris 3X
Kali iodatum 3X
Ruta graveolens 3X
Ammonium muriaticum 4X
Aconitum napellus 6X
Belladonna 6X
Bellis perennis 6X
Colocynthis 6X
Gnaphalium polycephalum 6X
Nux vomica 6X
Spigelia anthelmia 6X
Arsenicum album 12X
Causticum 12X
Hypericum perforatum 30X

QUESTIONS

Professional Formulas

PO Box 2034 Lake Oswego, OR 97035

INDICATIONS

For the temporary relief of minor pain radiating down the leg.*

PURPOSE

*Claims based on traditional homeopathic practice, not accepted medical evidence. Not FDA evaluated.

WARNINGS

In case of overdose, get medical help or contact a poison control center right away.

Keep out of the reach of children.

PREGNANCY OR BREAST FEEDING

If pregnant or breastfeeding, ask a healthcare professional before use.

DIRECTIONS

Place drops under tongue 30 minutes before/after meals. Adults and children 12 years and over: Take 10 drops up to 3 times per day for up to 6 weeks. For immediate onset of symptoms, take 10 to 15 drops every 15 minutes up to 3 hours. For less severe symptoms, take 10-15 drops hourly up to 8 hours. Consult a physician for use in children under 12 years of age.

OTHER INFORMATION

Tamper resistant. If seal is broken, do not use. After opening, close container tightly and store at room temperature away from heat.

INACTIVE INGREDIENTS

20% ethanol, purified water.

LABEL

Est 1985

Professional Formulas

Complementary Health

Sciatica Drops

Homeopathic Remedy

2 FL. OZ. (59 mL)